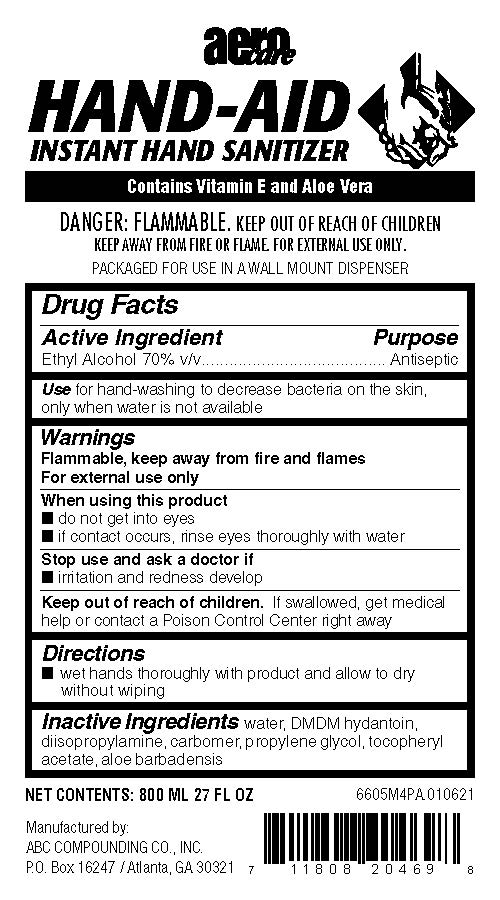 DRUG LABEL: Hand-Aid
NDC: 62257-122 | Form: GEL
Manufacturer: ABC Compounding Co., Inc.
Category: otc | Type: HUMAN OTC DRUG LABEL
Date: 20251119

ACTIVE INGREDIENTS: ALCOHOL 0.7 mL/1 mL
INACTIVE INGREDIENTS: CARBOMER 934; PROPYLENE GLYCOL; ALOE VERA LEAF; .ALPHA.-TOCOPHEROL ACETATE, DL-; DIISOPROPYLAMINE; DMDM HYDANTOIN; WATER

Hand-Aid 6605 Drug Facts and Label

Drug Facts Box OTC-Active Ingredient Section

Ethyl Alcohol 70% v/v

Drug Facts Box OTC-Purpose Section

Antiseptic

Drug Facts Box OTC-Indications & Usage Section

for hand-washing to decrease bacteria on the skin, only when water is not available

Drug Facts Box OTC-Warnings Section

FLAMMABLE, keep away from fire and flames

For external use only

Drug Facts Box OTC-When Using Section

do not get into eyes

if contact occurs, rinse eyes thoroughly with water

Drug Facts Box OTC-Stop Use Section

irritation and redness develop

Drug Facts Box OTC-Keep Out of Reach of Children Section

if swallowed, get medical help or contact a Poison Control Center right away

Drug Facts Box OTC-Dosage & Administration Section

wet hands thoroughly with product and allow to dry without wiping

Drug Facts Box OTC-Inactive Ingredient Section

water, DMDM hydantoin, diidopropylamine, carbomer, propylene glycol, tocopheryl acetate, aloe barbadensis,

Hand-Aid 6605 Drug Facts and Label

6605M4PA_Hand-Aid 800ml bag 1-15-2021